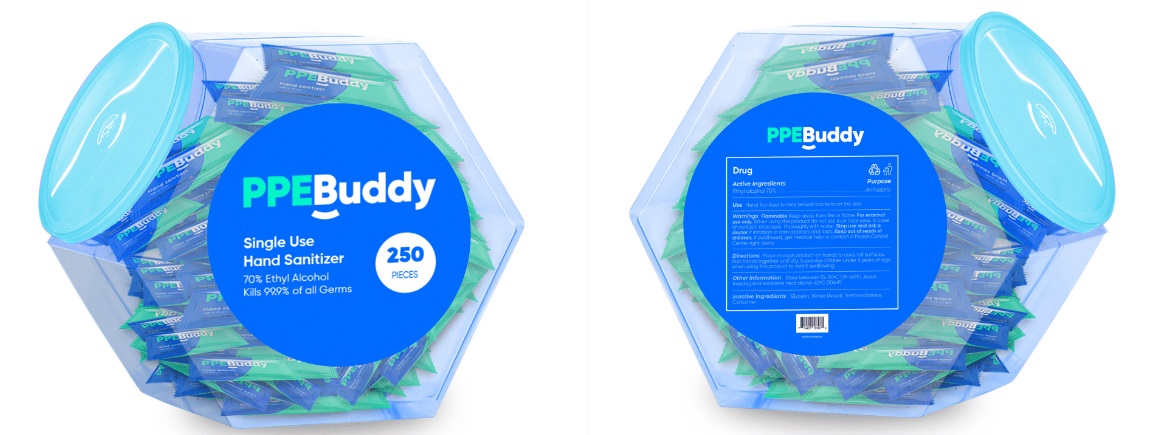 DRUG LABEL: PPEBuddy Single Use Hand Sanitizer Bucket S002
NDC: 79437-002 | Form: GEL
Manufacturer: PPE Buddy LLC
Category: otc | Type: HUMAN OTC DRUG LABEL
Date: 20200806

ACTIVE INGREDIENTS: ALCOHOL 0.7 mL/1 mL
INACTIVE INGREDIENTS: GLYCERIN; WATER; TROLAMINE; CARBOMER HOMOPOLYMER, UNSPECIFIED TYPE

PPEBuddy Single Use Hand Sanitizer Bucket

Active Ingredients

Ethyl alcohol 70%

Purpose

Antiseptic

Use

Hand Sanitizer to help reduce bacteria on the skin

Warnings

Flammable. Keep away from fire or flame.

For external use only.

When using this product

do not use in or near eyes. In case of contact, rinse eyes thoroughly with water.

Stop use and ask a doctor if

irritation or rash appears and lasts.

Keep out of reach of children.

If swallowed, get medical help or contact a Poison Control Center right away.

Directions:

Place enough product on hands to cover all surfaces. Rub hands together until dry. Supervise children under 6 years of age when using this product to avoid swallowing.

Other Information:

Store between 15-30°C (59-86°F). Avoid freezing and excessive heat above 40°C (104°F).

Inactive Ingredients:

Glycerin, Water (Aqua), Triethanolamine, Carbomer